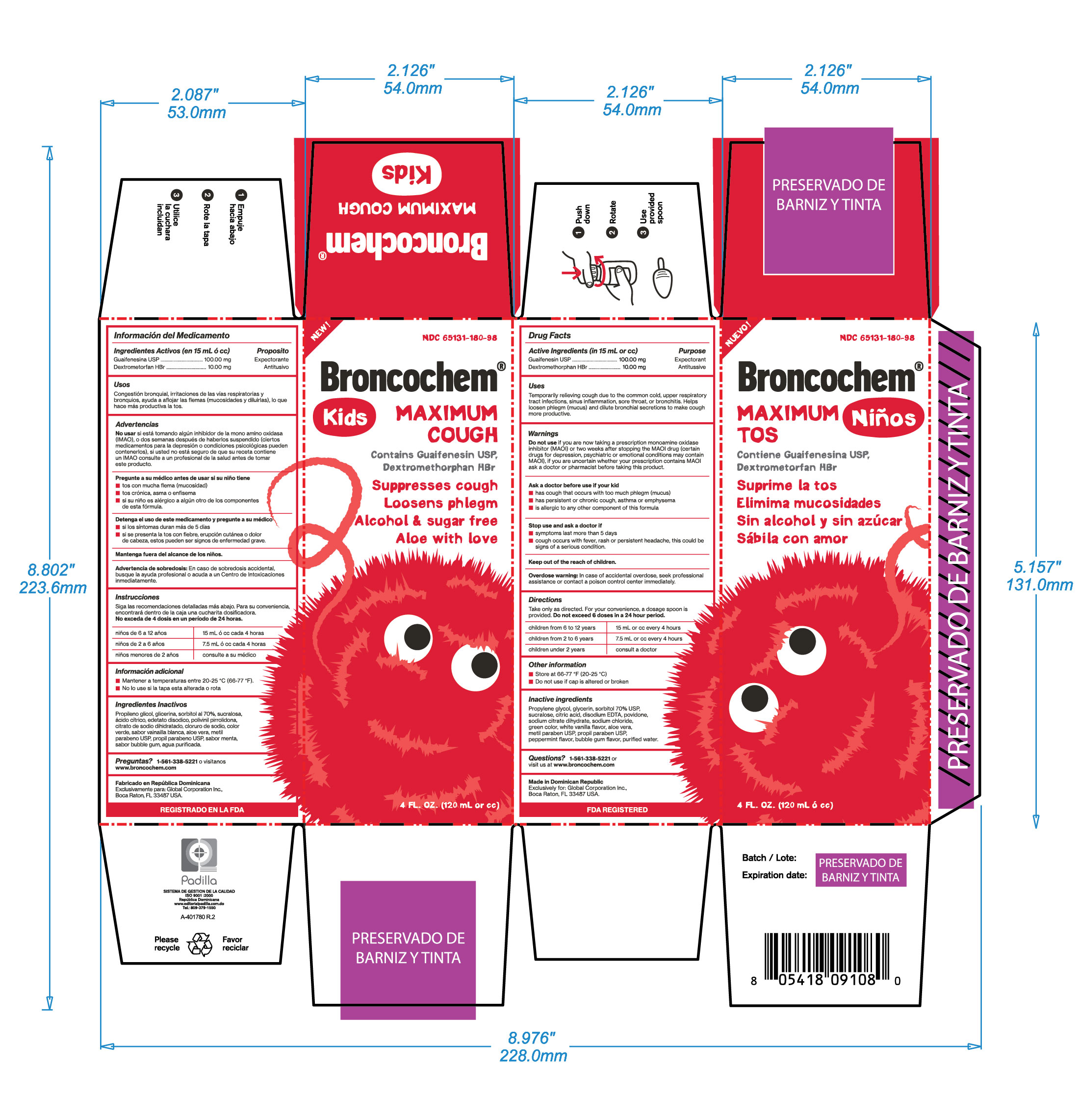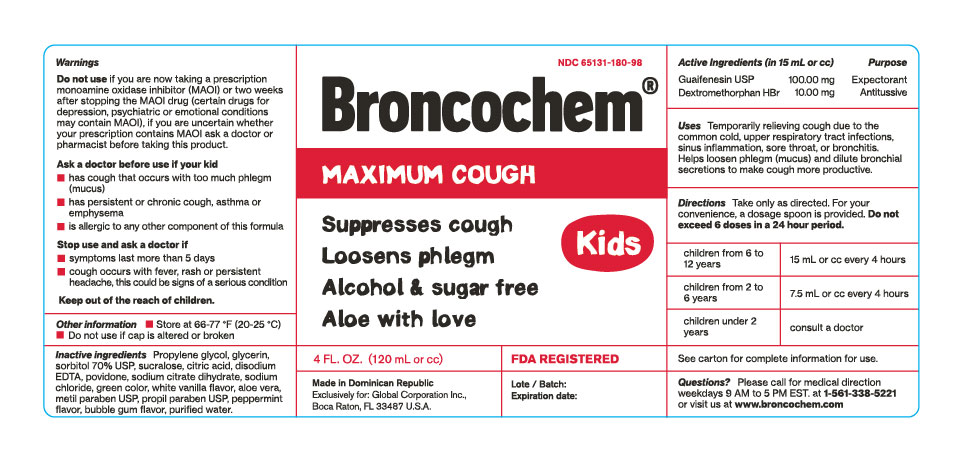 DRUG LABEL: BRONCOCHEM
NDC: 65131-180 | Form: SYRUP
Manufacturer: LABORATORIO MAGNACHEM INTERNATIONAL SRL
Category: otc | Type: HUMAN OTC DRUG LABEL
Date: 20250313

ACTIVE INGREDIENTS: DEXTROMETHORPHAN HYDROBROMIDE 10 mg/15 mL; GUAIFENESIN 100 mg/15 mL
INACTIVE INGREDIENTS: PROPYLENE GLYCOL 2.25 mL/15 mL; GLYCERIN 2.25 mL/15 mL; SORBITOL 2.25 mL/15 mL; SUCRALOSE 15 mg/15 mL; ANHYDROUS CITRIC ACID 45 mg/15 mL; DISODIUM HEDTA 1.35 mg/15 mL; POVIDONE K90 270 mg/15 mL; SODIUM CITRATE 45 mg/15 mL; SODIUM CHLORIDE 9.37 mg/15 mL; FD&C GREEN NO. 3 0.036 mg/15 mL; VANILLA 0.0006 mL/15 mL; ALOE VERA LEAF 30 mg/15 mL; METHYLPARABEN 15 mg/15 mL; PEPPERMINT 0.001 mL/15 mL; PROPYLPARABEN 2.25 mg/15 mL; WATER 15 mL/15 mL

BRONCOCHEM MAXIMUM COUGH KIDS

Warnings

Do not Use

If you are now taking a prescription monoamine oxidase inhibitor (MAOI) or two weeks after stopping the MAOI drug (certain drugs for depression, psychiatric or emotional conditions may contain MAOI), if you are uncertain whether your prescription contains MAOI ask a doctor or pharmacist before taking this product.

Uses

Temporarily relieves coug due to minor throat and Bronchial irritation occurring with common cold. Helps loosen phlegm (mucus) and dilute bronchial secretions to make cough more productive.

Active Ingredients

Guaifenesin........................100.00mg

Dextromethorphan HBr........10.00mg

Ask a doctor before use if your kid have

Cough that occurs with too much phlegm (mucus)

Persistent or chronic cough, asthma or emphysema

If your kid is allergic to any other component of this formula

Stop use and ask a doctor if

Symptoms last more than 5 days

Cough occurs with fever, rash or persistent headache, this could be signs of a serious condition

keep out of the reach od children

Keep out of the reach of children

Overdose Warnigs

In case of accidental overdose, seek professional assistance or contact a poison control center immediately

Directions

Take only as directed, for your convinience a dosage spoon is provided. Do not excees 6 doses in a 24 hour period

Children from 6 to 12 years------15mL or cc every 4 hours

Children from 2 to 6 years-------7.5mL or ccevery 4 hours

Children under 2 years, ask your doctor

Other Information

Store al 66-77

Inactive Ingredients

Propylene glycol, Glycerin, Sorbitol 70%, Povidone, Sodium Citrate Dihydrate, Sodium Chloride,

Green color, White Vanilla Flavor, Aloe Vera, Methy Paraben USP, Propil Paraben USP. Peppermint Flavor, Bubble Gum Flavor, Purified Water

Quiestions

1-561-338-5221 or visit us at www.broncochem.com

Purpose

Guaifenesin........................Expectorant

Dextromethorphan HBr.........Antotussive